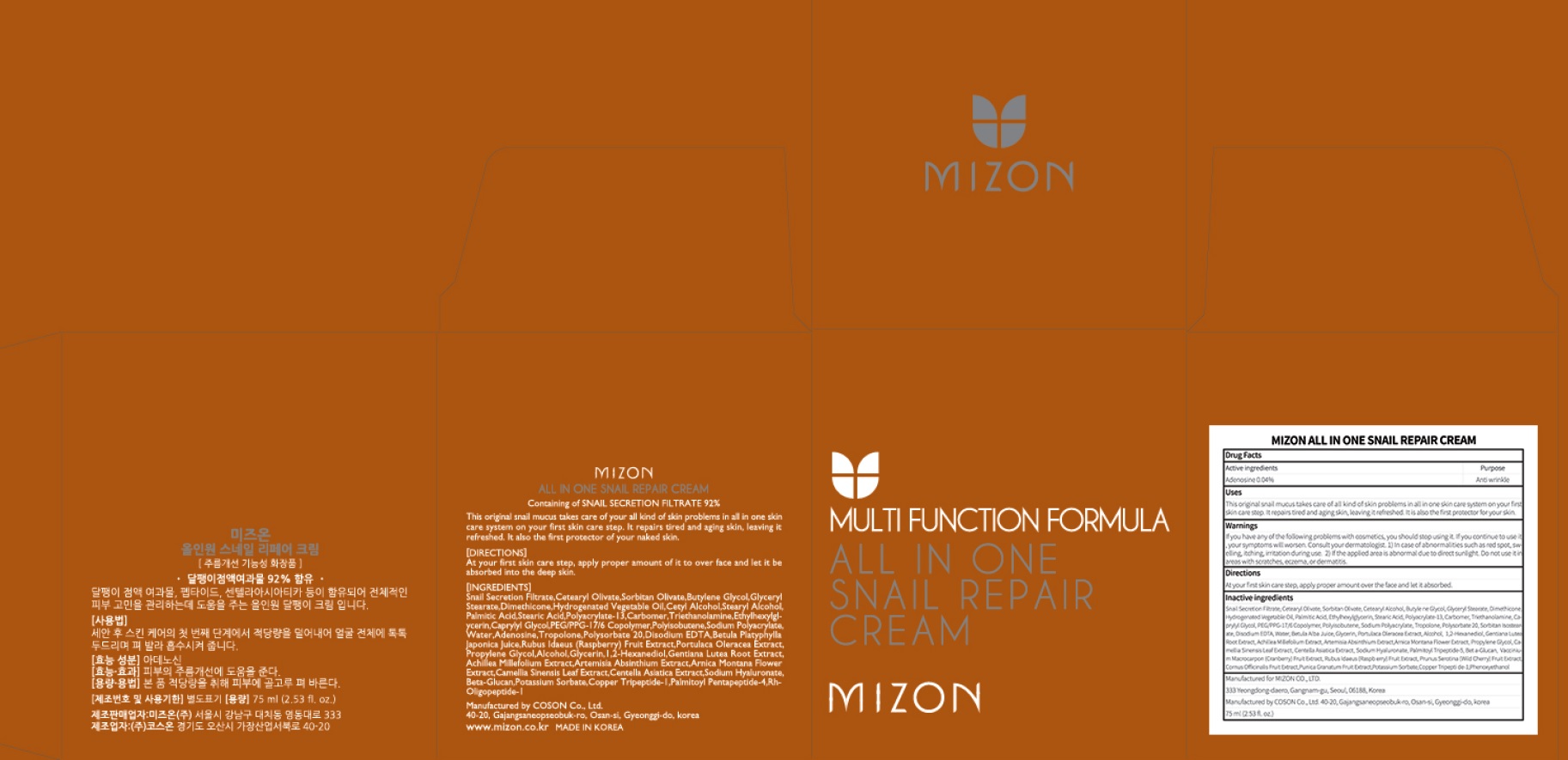 DRUG LABEL: MIZON ALL IN ONE SNAIL REPAIR CREA M
NDC: 57718-330 | Form: CREAM
Manufacturer: MIZON CO.,LTD.
Category: otc | Type: HUMAN OTC DRUG LABEL
Date: 20180726

ACTIVE INGREDIENTS: Adenosine 0.03 g/75 mL
INACTIVE INGREDIENTS: Butylene Glycol; Dimethicone

ACTIVE INGREDIENT

Active ingredients: Adenosine 0.04%

INACTIVE INGREDIENT

Inactive ingredients:

Snail Secretion Filtrate,Cetearyl Olivate,Sorbitan Olivate,Cetearyl Alcohol,Butylene Glycol,Glyceryl Stearate,Dimethicone,Hydrogenated Vegetable Oil,Palmitic Acid,Ethylhexylglycerin,Stearic Acid,Polyacrylate-13,Carbomer,Triethanolamine, Caprylyl Glycol,PEG/PPG-17/6 Copolymer,Polyisobutene,Sodium Polyacrylate,Tropolone,Polysorbate 20,Sorbitan Isostearate,Disodium EDTA,Water, Betula Alba Juice,Glycerin,Portulaca Oleracea Extract,Alcohol,1,2-Hexanediol,G entiana Lutea Root Extract,Achillea Millefolium Extract,Artemisia Absinthium Ex tract,Arnica Montana Flower Extract,Propylene Glycol,Camellia Sinensis Leaf Ex tract,Centella Asiatica Extract,Sodium Hyaluronate,Palmitoyl Tripeptide-5,Bet a-Glucan,Vaccinium Macrocarpon (Cranberry) Fruit Extract,Rubus Idaeus (Raspb erry) Fruit Extract,Prunus Serotina (Wild Cherry) Fruit Extract,Cornus Officinalis Fruit Extract,Punica Granatum Fruit Extract,Potassium Sorbate,Copper Tripepti de-1,Phenoxyethanol

PURPOSE

Purpose: Anti wrinkle

WARNINGS

If you have any of the following problems with cosmetics, you should stop using it. If you continue to use it, your symptoms will worsen. Consult your dermatologist. 1) In case of abnormalities such as red spot, swelling, itching, irritation during use. 2) If the applied area is abnormal due to direct sunlight. Do not use it in areas with scratches, eczema, or dermatitis.

KEEP OUT OF REACH OF CHILDREN

Uses

This original snail mucus takes care of all kind of skin problems in all in one skin care system on your first skin care step. It repairs tired and aging skin, leaving it refreshed. It is also the first protector for your skin.

Directions

At your first skin care step, apply proper amount over the face and let it absorbed.